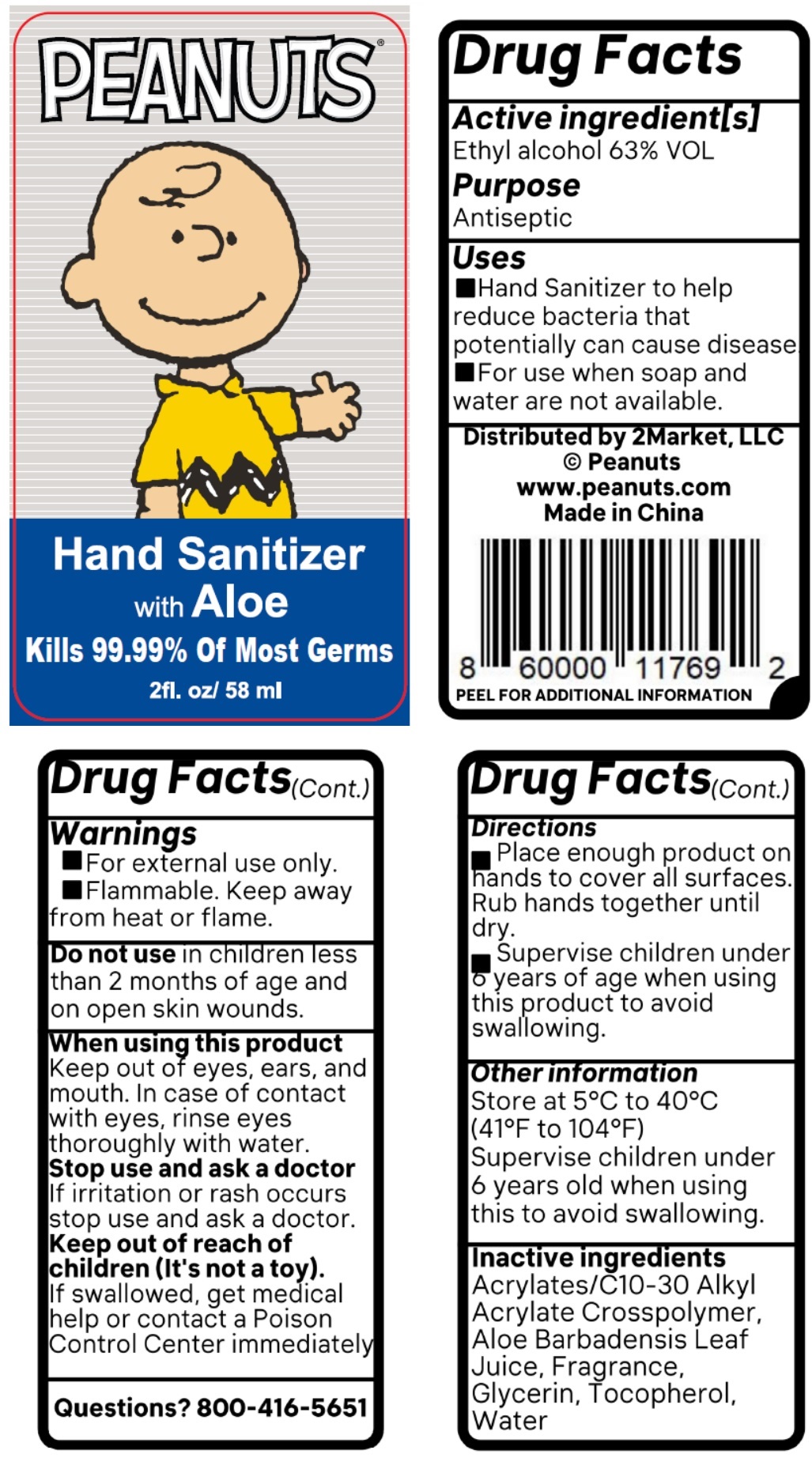 DRUG LABEL: PEANUTS
NDC: 76866-003 | Form: LIQUID
Manufacturer: 2 Market Llc
Category: otc | Type: HUMAN OTC DRUG LABEL
Date: 20200504

ACTIVE INGREDIENTS: ALCOHOL 63 mL/100 mL
INACTIVE INGREDIENTS: CARBOMER INTERPOLYMER TYPE A (ALLYL SUCROSE CROSSLINKED); ALOE VERA LEAF; GLYCERIN; TOCOPHEROL; WATER

PEANUTS® Hand Sanitizer with Aloe

Active ingredient[s]

Ethyl alcohol 63% VOL

Purpose

Antiseptic

Uses

■ Hand Sanitizer to help reduce bacteria that potentially can cause disease.

■ For use when soap and water are not available.

Warnings

■ For external use only.

■ Flammable. Keep away from heat or flame.

Do not use in children less than 2 months of age and on open skin wounds.

When using this product

Keep out of eyes, ears, and mouth. In case of contact with eyes, rinse eyes thoroughly with water.

Stop use and ask a doctor

If irritation or rash occurs stop use and ask a doctor.

Keep out of reach of children (It's not a toy).

If swallowed, get medical help or contact a Poison Control Center immediately.

Questions? 800-416-5651

Directions

■ Place enough product on hands to cover all surfaces. Rub hands together until dry.

■ Supervise children under 6 years of age when using this product to avoid swallowing.

Other information

Store at 5°C to 40°C (41°F to 104°F)

Supervise children under 6 years old when using this to avoid swallowing.

Inactive ingredients

Acrylates/C10-30 Alkyl Acrylate Crosspolymer, Aloe Barbadensis Leaf Juice, Fragrance, Glycerin, Tocopherol, Water

Kills 99.99% Of Most Germs

Distributed by 2Market, LLC

© Peanuts

www.peanuts.com

Made in China